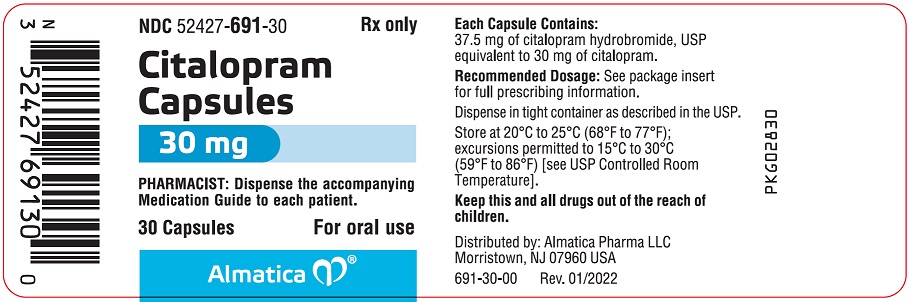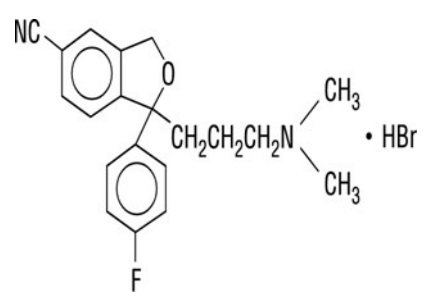 DRUG LABEL: citalopram
NDC: 52427-691 | Form: CAPSULE
Manufacturer: Almatica Pharma LLC
Category: prescription | Type: HUMAN PRESCRIPTION DRUG LABEL
Date: 20251007

ACTIVE INGREDIENTS: CITALOPRAM HYDROBROMIDE 30 mg/1 1
INACTIVE INGREDIENTS: COPOVIDONE K25-31; CROSCARMELLOSE SODIUM; GELATIN, UNSPECIFIED; MAGNESIUM STEARATE; MICROCRYSTALLINE CELLULOSE; TALC; TITANIUM DIOXIDE; FD&C BLUE NO. 1; FD&C RED NO. 3

HIGHLIGHTS OF PRESCRIBING INFORMATION

These highlights do not include all the information needed to use CITALOPRAM CAPSULES safely and effectively. See full prescribing information for CITALOPRAM CAPSULES.
CITALOPRAM capsules, for oral use
Initial U.S. Approval: 1998

RECENT MAJOR CHANGES

Warnings and Precautions (5.3, 5.4) | 8/2023

WARNING: SUICIDAL THOUGHTS AND BEHAVIORS

See full prescribing information for complete boxed warning.

Increased risk of suicidal thoughts and behaviors in pediatric and young adult patients taking antidepressants. Closely monitor all antidepressant-treated patients for clinical worsening and emergence of suicidal thoughts and behaviors (5.1). Citalopram Capsules is not approved for use in pediatric patients (8.4).

1 INDICATIONS AND USAGE

Citalopram Capsules is a selective serotonin reuptake inhibitor (SSRI) indicated for treatment of Major Depressive Disorder (MDD) in adults. (1)

2 DOSAGE AND ADMINISTRATION

- Do not initiate treatment with Citalopram Capsules. Use another citalopram product for initial dosage titration or dosages other than 30 mg once daily. (2.1)
- Administer once daily with or without food. (2.1)
- Recommended dosage of Citalopram Capsules is 30 mg once daily. (2.1)
- Citalopram dosages above 40 mg once daily are not recommended due to the risk of QT prolongation. (2.1)
- When discontinuing Citalopram Capsules, reduce dose gradually. Gradual dosage reduction will require use of another citalopram product. (2.4, 5.6)

3 DOSAGE FORMS AND STRENGTHS

- Capsules: 30 mg (3)

4 CONTRAINDICATIONS

- Concomitant use of monoamine oxidase inhibitors (MAOIs) or use within 14 days of discontinuing an MAOI. (4)
- Concomitant use of pimozide. (4)
- Known hypersensitivity to citalopram or any of the inactive ingredients of Citalopram Capsules. (4)

5 WARNINGS AND PRECAUTIONS

- QT Prolongation and Torsade de Pointes: Dose-dependent QTc prolongation, Torsade de pointes, ventricular tachycardia, and sudden death have occurred. Avoid use of Citalopram Capsules in patients with congenital long QT syndrome, bradycardia, hypokalemia or hypomagnesemia, recent acute myocardial infarction, or uncompensated heart failure and patients taking other drugs that prolong the QTc interval. Monitor electrolytes in patients at high risk for hypokalemia or hypomagnesemia. Discontinue Citalopram Capsules in patients with persistent QTc measurements > 500 ms. (5.2, 7)
- Serotonin Syndrome: Increased risk when co-administered with other serotonergic agents, but also when taken alone. If it occurs, discontinue Citalopram Capsules and serotonergic agents and initiate supportive treatment (4, 5.3, 7)
- Increased Risk of Bleeding: Concomitant use of aspirin, nonsteroidal anti-inflammatory drugs, other antiplatelet drugs, warfarin, and other anticoagulants may increase this risk. (5.4)
- Activation of Mania or Hypomania: Screen patients for bipolar disorder. (5.5)
- Discontinuation Syndrome: When discontinuing Citalopram Capsules, reduce dosage gradually and monitor for discontinuation symptoms. Gradual reduction will require use of another citalopram product. (5.6)
- Seizures: Use with caution in patients with seizure disorder. (5.7)
- Angle Closure Glaucoma: Avoid use of Citalopram Capsules in patients with untreated anatomically narrow angles treated. (5.8)
- Hyponatremia: Can occur in association with syndrome of inappropriate antidiuretic hormone secretion. (5.9)
- Sexual Dysfunction: Citalopram Capsules may cause symptoms of sexual dysfunction. (5.10)

6 ADVERSE REACTIONS

Most commonly observed adverse reactions (incidence at least twice the incidence of placebo) are: fever, arthalgia, myalgia, anorexia, agitation, yawning, sinusitis, ejaculation disorder (primarily ejaculatory delay), decreased libido, and impotence (6.1).

To report SUSPECTED ADVERSE REACTIONS, contact Almatica Pharma LLC at 1-877-447-7979, or FDA at 1-800-FDA-1088 or www.fda.gov/medwatch.

7 DRUG INTERACTIONS

- CYP2C19 inhibitors and CYP2C19 poor metabolizers: Avoid concomitant use. There is an increased risk of QT prolongation with concomitant use. (7)

8 USE IN SPECIFIC POPULATIONS

- Pregnancy: SSRI use, particularly late in pregnancy, may increase the risk for persistent pulmonary hypertension and symptoms of poor adaptation (respiratory distress, temperature instability, feeding difficulties, hypotonia, tremor, irritability) in the neonate. (8.1)
- Elderly patients: Not recommended. (8.5)
- Hepatic Impairment: Not recommended. (8.6)

FULL PRESCRIBING INFORMATION

WARNING: SUICIDAL THOUGHTS AND BEHAVIORS

Antidepressants increased the risk of suicidal thoughts and behavior in pediatric and young adult patients in short-term studies. Closely monitor all antidepressant-treated patients for clinical worsening, and for emergence of suicidal thoughts and behaviors [see Warnings and Precautions (5.1)]. Citalopram Capsules is not approved for use in pediatric patients [see Use in Specific Populations (8.4)].

1 INDICATIONS AND USAGE

Citalopram Capsules are indicated for the treatment of Major Depressive Disorder (MDD) in adults [see Clinical Studies (14)].

2 DOSAGE AND ADMINISTRATION

2.1 Recommended Dosage

Do not initiate treatment with Citalopram Capsules because the only available dose strength is 30 mg. Use another citalopram product for initial dosage, titration, and dosages other than 30 mg once daily. Refer to Prescribing Information of the other citalopram products for the recommended dosage for those products.

Administer Citalopram Capsules orally, once daily, with or without food.

Citalopram should be administered at an initial dose of 20 mg once daily, with an increase to a maximum dose of 40 mg once daily at an interval of no less than one week. Citalopram dosages above 40 mg once daily are not recommended due to the risk of QT prolongation [see Warnings and Precautions (5.2)].

2.2 Screen for Bipolar Disorder Prior to Starting Citalopram Capsules

Prior to initiating treatment with Citalopram Capsules or another antidepressant, screen patients for a personal or family history of bipolar disorder, mania, or hypomania [see Warnings and Precautions (5.5)].

2.3 Switching Patients to or from a Monoamine Oxidase Inhibitor Antidepresssant

At least 14 days must elapse between discontinuation of an monoamine oxidase inhibitor (MAOI) and initiation of therapy with Citalopram Capsules. Conversely, at least 14 days must elapse after stopping Citalopram Capsules before starting an MAOI antidepressant [see Contraindications (4), Warnings and Precautions (5.3)].

2.4 Discontinuing Treatment with Citalopram Capsules

Adverse reactions may occur upon discontinuation of Citalopram Capsules [see Warnings and Precautions (5.6)]. Gradually reduce the dosage rather than stopping Citalopram Capsules abruptly whenever possible. Given that 30 mg is only available dosage strength of Citalopram Capsules, gradual dosage reduction will require the use of another citalopram product.

3 DOSAGE FORMS AND STRENGTHS

30 mg: Hard shell gelatin capsules, with “ALM” printed axially on the blue opaque cap in black ink and “691” printed axially on the white opaque body in black ink.

Citalopram Capsules dosage strength is based on the active moiety, citalopram.

4 CONTRAINDICATIONS

Citalopram Capsules is contraindicated in patients:

- taking, or within 14 days of stopping, MAOIs (including MAOIs such as linezolid or intravenous methylene blue) because of an increased risk of serotonin syndrome [see Warnings and Precautions (5.3), Drug Interactions (7)].
- taking pimozide because of risk of QT prolongation [see Drug Interactions (7)].
- with known hypersensitivity to citalopram or any of the inactive ingredients in Citalopram Capsules. Reactions have included angioedema and anaphylaxis [see Adverse Reactions (6.2)].

5 WARNINGS AND PRECAUTIONS

5.1 Suicidal Thoughts and Behaviors in Adolescent and Young Adults

In pooled analyses of placebo-controlled trials of antidepressant drugs (SSRIs and other antidepressant classes) that included approximately 77,000 adult patients and over 4,500 pediatric patients, the incidence of suicidal thoughts and behaviors in antidepressant-treated patients age 24 years and younger was greater than in placebo-treated patients. There was considerable variation in risk of suicidal thoughts and behaviors among drugs, but there was an increased risk identified in young patients for most drugs studied. There were differences in absolute risk of suicidal thoughts and behaviors across the different indications, with the highest incidence in patients with MDD. These drug-placebo differences in the number of cases of suicidal thoughts and behaviors per 1,000 patients treated are provided in Table 1.

Table 1: Risk Differences of the Number of Patients with Suicidal Thoughts or Behavior in the Pooled Placebo-Controlled Trials of Antidepressants in Pediatric* and Adult Patients
Age Range | Drug-Placebo Difference in Number of Patients* with Suicidal Thoughts or Behaviors per 1,000 Patients Treated
 | Increases Compared to Placebo
<18 years old | 14 additional cases
18 to 24 years old | 5 additional cases
 | Decreases Compared to Placebo
25 to 64 years old | 1 fewer case
≥65 years old | 6 fewer cases
*Citalopram Capsules is not approved for use in pediatric patients.

It is unknown whether the risk of suicidal thoughts and behaviors in children, adolescents, and young adults extends to longer-term use, i.e., beyond four months. However, there is substantial evidence from placebo-controlled maintenance trials in adults with MDD that antidepressants delay the recurrence of depression and that depression itself is a risk factor for suicidal thoughts and behaviors.

Monitor all antidepressant-treated patients for any indication for clinical worsening and emergence of suicidal thoughts and behaviors, especially during the initial few months of drug therapy, and at times of dosage changes. Counsel family members or caregivers of patients to monitor for changes in behavior and to alert the healthcare provider. Consider changing the therapeutic regimen, including possibly discontinuing Citalopram Capsules, in patients whose depression is persistently worse, or who are experiencing emergent suicidal thoughts or behaviors.

5.2 QT-Prolongation and Torsade de Pointes

Citalopram causes dose-dependent QTc prolongation, an ECG abnormality that has been associated with Torsade de Pointes (TdP), ventricular tachycardia, and sudden death, all of which have been observed in postmarketing reports for citalopram [see Adverse Reactions 6.2)].

Because of the risk of QTc prolongation at higher citalopram doses, it is recommended that citalopram should not be given at doses above 40 mg/day [see Clinical Pharmacology (12.2)].

Avoid use of Citalopram Capsules in CYP2C19 poor metabolizers, patients receiving concomitant cimetidine or another CYP2C19 inhibitor, patients with hepatic impairment, and patients who are greater than 60 years of age, because Citalopram Capsules are only available in a 30 mg dose strength and dosage adjustments are not possible [see Drug Interactions (7), Use in Specific Populations (8.5, 8.6), Clinical Pharmacology (12.3)].

Citalopram should be avoided in patients with congenital long QT syndrome, bradycardia, hypokalemia or hypomagnesemia, recent acute myocardial infarction, or uncompensated heart failure unless the benefits outweigh the risks for a particular patient. Citalopram should also not be used in patients who are taking other drugs that prolong the QTc interval [see Drug Interactions (7)]. Such drugs include Class 1A (e.g., quinidine, procainamide) or Class III (e.g., amiodarone, sotalol) antiarrhythmic medications, antipsychotic medications (e.g., chlorpromazine, thioridazine), antibiotics (e.g., gatifloxacin, moxifloxacin), or any other class of medications known to prolong the QTc interval (e.g., pentamidine, levomethadyl acetate, methadone).

Electrolyte and/or ECG monitoring is recommended in certain circumstances. Patients being considered for citalopram treatment who are at risk for significant electrolyte disturbances should have baseline serum potassium and magnesium measurements with periodic monitoring. Hypokalemia (and/or hypomagnesemia) may increase the risk of QTc prolongation and arrhythmia, and should be corrected prior to initiation of treatment and periodically monitored. ECG monitoring is recommended in patients for whom citalopram use is not recommended unless the benefits clearly outweigh the risks for a particular patient (see above). These include those patients with the cardiac conditions noted above, and those taking other drugs that may prolong the QTc interval.

Discontinue Citalopram Capsules in patients who are found to have persistent QTc measurements >500 ms. If patients taking Citalopram Capsules experience symptoms that could indicate the occurrence of cardiac arrhythmias, e.g., dizziness, palpitations, or syncope, the prescriber should initiate further evaluation, including cardiac monitoring.

5.3 Serotonin Syndrome

SSRIs, including Citalopram Capsules, can precipitate serotonin syndrome, a potentially life-threatening condition. The risk is increased with concomitant use of other serotonergic drugs (including triptans, tricyclic antidepressants, fentanyl, lithium, tramadol, meperidine, methadone, tryptophan, buspirone, amphetamines, and St. John’s Wort) and with drugs that impair metabolism of serotonin, i.e., MAOIs [see Contraindications (4), Drug Interactions (7)]. Serotonin syndrome can also occur when these drugs are used alone.

Serotonin syndrome symptoms may include mental status changes (e.g., agitation, hallucinations, delirium, and coma), autonomic instability (e.g., tachycardia, labile blood pressure, dizziness, diaphoresis, flushing, hyperthermia), neuromuscular symptoms (e.g., tremor, rigidity, myoclonus, hyperreflexia, incoordination), seizures, and gastrointestinal symptoms (e.g., nausea, vomiting, diarrhea).

The concomitant use of Citalopram Capsules with MAOIs is contraindicated. In addition, do not initiate Citalopram Capsules in a patient being treated with MAOIs such as linezolid or intravenous methylene blue. No reports involved the administration of methylene blue by other routes (such as oral tablets or local tissue injection). If it is necessary to initiate treatment with an MAOI such as linezolid or intravenous methylene blue in a patient taking Citalopram Capsules, discontinue Citalopram Capsules before initiating treatment with the MAOI [see Contraindications (4), Drug Interactions (7)].

Monitor all patients taking Citalopram Capsules for the emergence of serotonin syndrome. Discontinue treatment with Citalopram Capsules and any concomitant serotonergic agents immediately if the above symptoms occur, and initiate supportive symptomatic treatment. If concomitant use of Citalopram Capsules with other serotonergic drugs is clinically warranted, inform patients of the increased risk for serotonin syndrome and monitor for symptoms.

5.4 Increased Risk of Bleeding

Drugs that interfere with serotonin reuptake inhibition, including Citalopram Capsules, increase the risk of bleeding events. Concomitant use of aspirin, nonsteroidal anti-inflammatory drugs (NSAIDS), antiplatelet drugs, warfarin, and other anticoagulants may add to this risk. Case reports and epidemiological studies (case-control and cohort design) have demonstrated an association between use of drugs that interfere with serotonin reuptake and the occurrence of gastrointestinal bleeding. Based on data from the published observational studies, exposure to SSRIs, particularly in the month before delivery, has been associated with a less than 2-fold increase in the risk of postpartum hemorrhage [see Use in Specific Populations (8.1)]. Bleeding events related to drugs that interfere with serotonin reuptake have ranged from ecchymosis, hematoma, epistaxis, and petechiae to life-threatening hemorrhages.

Inform patients about the increased risk of bleeding associated with the concomitant use of Citalopram Capsules and antiplatelet agents or anticoagulants. For patients taking warfarin, carefully monitor the international normalized ratio [see Drug Interactions (7)].

5.5 Activation of Mania or Hypomania

In patients with bipolar disorder, treating a depressive episode with Citalopram Capsules or another antidepressant may precipitate a mixed/manic episode. In controlled clinical trials with another citalopram product, patients with bipolar disorder were excluded; however, symptoms of mania or hypomania were reported in 0.1% of undiagnosed patients treated with the citalopram product. Prior to initiating treatment with Citalopram Capsules, screen patients for any personal or family history of bipolar disorder, mania, or hypomania [see Dosage and Administration (2.2)].

5.6 Discontinuation Syndrome

Adverse reactions after discontinuation of serotonergic antidepressants, particularly after abrupt discontinuation, include: nausea, sweating, dysphoric mood, irritability, agitation, dizziness, sensory disturbances (e.g., paresthesia, such as electric shock sensations), tremor, anxiety, confusion, headache, lethargy, emotional lability, insomnia, hypomania, tinnitus, and seizures. A gradual reduction in dosage rather than abrupt cessation is recommended whenever possible [see Dosage and Administration (2.4)].

5.7 Seizures

Citalopram has not been systematically evaluated in patients with seizure disorders. Patients with a history of seizures were excluded from clinical studies. In clinical trials of another citalopram product, seizures occurred in 0.3% of patients treated with citalopram (a rate of one patient per 98 years of exposure) and 0.5% of patients treated with placebo (a rate of one patient per 50 years of exposure). Citalopram Capsules should be prescribed with caution in patients with a seizure disorder.

5.8 Angle Closure Glaucoma

The pupillary dilation that occurs following use of many antidepressant drugs, including citalopram, may trigger an angle closure attack in a patient with anatomically narrow angles who does not have a patent iridectomy. Avoid use of antidepressants, including Citalopram Capsules, in patients with untreated anatomically narrow angles.

5.9 Hyponatremia

Hyponatremia may occur as a result of treatment with SSRIs, including Citalopram Capsules. Cases with serum sodium lower than 110 mmol/L have been reported with another citalopram product. Signs and symptoms of hyponatremia include headache, difficulty concentrating, memory impairment, confusion, weakness, and unsteadiness, which may lead to falls. Signs and symptoms associated with more severe and/or acute cases have included hallucination, syncope, seizure, coma, respiratory arrest, and death. In many cases, this hyponatremia appears to be the result of the syndrome of inappropriate antidiuretic hormone secretion (SIADH).

In patients with symptomatic hyponatremia, discontinue Citalopram Capsules and institute appropriate medical intervention. Elderly patients, patients taking diuretics, and those who are volume depleted may be at greater risk for developing hyponatremia with SSRIs [see Use in Specific Populations (8.5)].

5.10 Sexual Dysfunction

Use of SSRIs, including Citalopram Capsules, may cause symptoms of sexual dysfunction [see Adverse Reactions (6.1)]. In male patients, SSRI use may result in ejaculatory delay or failure, decreased libido, and erectile dysfunction. In female patients, SSRI use may result in decreased libido and delayed or absent orgasm.

It is important for prescribers to inquire about sexual function prior to initiation of Citalopram Capsules and to inquire specifically about changes in sexual function during treatment, because sexual function may not be spontaneously reported. When evaluating changes in sexual function, obtaining a detailed history (including timing of symptom onset) is important because sexual symptoms may have other causes, including the underlying psychiatric disorder. Discuss potential management strategies to support patients in making informed decisions about treatment.

6 ADVERSE REACTIONS

The following adverse reactions are discussed in greater detail in other sections of the labeling:

- Hypersensitivity reactions [see Contraindications (4)]
- Suicidal Thoughts and Behaviors in Adolescent and Young Adults [see Warnings and Precautions (5.1)]
- QT-Prolongation and Torsade de Pointes [see Warnings and Precautions (5.2)]
- Serotonin Syndrome [see Warnings and Precautions (5.3)]
- Increased Risk of Bleeding [see Warnings and Precautions (5.4)]
- Activation of Mania or Hypomania [see Warnings and Precautions (5.5)]
- Discontinuation Syndrome [see Warnings and Precautions (5.6)]
- Seizures [see Warnings and Precautions (5.7)]
- Angle Closure Glaucoma [see Warnings and Precautions (5.8)]
- Hyponatremia [see Warnings and Precautions (5.9)]
- Sexual Dysfunction [see Warnings and Precautions (5.10)]

6.1 Clinical Trials Experience

Because clinical studies are conducted under widely varying conditions, adverse reaction rates observed in the clinical studies of a drug cannot be directly compared to rates in the clinical studies of another drug and may not reflect the rates observed in practice.

The safety of Citalopram Capsules for the treatment for major depressive disorder (MDD) in adults is based upon adequate and well-controlled studies of another citalopram product. The results of these adequate and well-controlled studies of citalopram are presented below.

The safety for citalopram included exposures in patients and/or healthy subjects from 3 different groups of studies: 429 healthy subjects in clinical pharmacology/ pharmacokinetic studies; 4,422 exposures from patients in controlled and uncontrolled clinical trials, corresponding to approximately 1,370 patient-exposure years. There were, in addition, over 19,000 exposures from mostly open-label, European postmarketing studies. The conditions and duration of treatment with citalopram varied greatly and included (in overlapping categories) open-label and double-blind studies, inpatient and outpatient studies, fixed-dose and dose-titration studies, and short-term and long-term exposure.

Adverse Reactions Associated with Discontinuation of Treatment

Among 1,063 patients with MDD who received citalopram at doses ranging from 10 mg to 80 mg once daily in placebo-controlled trials of up to 6 weeks in duration, 16% discontinued treatment due to an adverse reaction, as compared to 8% of 446 patients receiving placebo. The adverse reactions associated with discontinuation (i.e., associated with discontinuation in at least 1% of citalopram-treated patients at a rate at least twice that of placebo) are shown in Table 2.

Table 2: Adverse Reactions Associated with Discontinuation of Treatment in Short-Term, Placebo-Controlled, Depression Trials

Body System/Adverse Reaction | Citalopram* (N=1,063) % | Placebo (N=446) %
General
Asthenia | 1 | <1
Gastrointestinal Disorders
Nausea | 4 | 0
Dry Mouth | 1 | <1
Vomiting | 1 | 0
Central and Peripheral Nervous System Disorders
Dizziness | 2 | <1
Psychiatric Disorders
Insomnia | 3 | 1
Somnolence | 2 | 1
Agitation | 1 | <1
* A patient can report more than one reason for discontinuation and be counted more than once in this table.

Table 3 enumerates adverse reactions that occurred among 1,063 patients with MDD who received citalopram at doses ranging from 10 mg to 80 mg once daily in placebo-controlled trials of up to 6 weeks in duration.

The most common adverse reaction that occurred in citalopram-treated patients with an incidence of 5% or greater and at least twice the incidence in placebo patients was ejaculation disorder (primarily ejaculatory delay) in male patients, see Table 3.

Table 3: Adverse Reactions (≥2% and Greater than Placebo) Among Citalopram-treated Patients*

Body System/Adverse Reaction | Citalopram; (N=1,063); % | Placebo; (N=446); %
Gastrointestinal Disorders
Nausea | 21 | 14
Diarrhea | 8 | 5
Dyspepsia | 5 | 4
Vomiting | 4 | 3
Abdominal Pain | 3 | 2
Autonomic Nervous System Disorders
Dry Mouth | 20 | 14
Sweating Increased | 11 | 9
Psychiatric Disorders
Somnolence | 18 | 10
Insomnia | 15 | 14
Anxiety | 4 | 3
Anorexia | 4 | 2
Agitation | 3 | 1
Dysmenorrhea^1 | 3 | 2
Libido Decreased | 2 | <1
Yawning | 2 | <1
Central & Peripheral Nervous System Disorders
Tremor | 8 | 6
Urogenital
Ejaculation Disorder^2,3 | 6 | 1
Impotence^3 | 3 | <1
Respiratory System Disorders
Upper Respiratory Tract Infection | 5 | 4
Rhinitis | 5 | 3
Sinusitis | 3 | <1
General
Fatigue | 5 | 3
Fever | 2 | <1
Musculoskeletal System Disorders
Arthralgia | 2 | 1
Myalgia | 2 | 1
* Except for the following adverse reactions which had an incidence on placebo. Citalopram: headache, asthenia, dizziness, constipation, palpitation, vision abnormal, sleep disorder, nervousness, pharyngitis, micturition disorder, back pain.
^1 Denominator used was for females only (N=638 citalopram; N=252 placebo).
^2 Primarily ejaculatory delay.
^3 Denominator used was for males only (N=425 citalopram; N=194 placebo).

Dose Dependency of Adverse Reactions

The potential relationship between the dose of citalopram administered and the incidence of adverse reactions was examined in a fixed-dose study in depressed patients receiving placebo or citalopram 10 mg, 20 mg, 40 mg, and 60 mg (1.5 times the maximum recommended dosage of citalopram). A positive dose response (p<0.05) for the following adverse reactions: fatigue, impotence, insomnia, sweating increased, somnolence, and yawning.

Male and Female Sexual Dysfunction with SSRIs

Although changes in sexual desire, sexual performance, and sexual satisfaction often occur as manifestations of a psychiatric disorder, they may also be a consequence of SSRI treatment. However, reliable estimates of the incidence and severity of untoward experiences involving sexual desire, performance, and satisfaction are difficult to obtain, in part because patients and health care providers may be reluctant to discuss them. Accordingly, estimates of the incidence of untoward sexual experience and performance cited in product labeling are likely to underestimate their actual incidence.

Table 4 below displays the incidence of sexual side effects reported by at least 2% of male patients taking citalopram in a pool of placebo-controlled clinical trials in patients with depression.

Table 4: Adverse Reactions (≥2%) Related to Sexual Dysfunction in Citalopram-treated Male Patients in Pooled Placebo-Controlled Clinical Trials of MDD

Treatment | Citalopram | Placebo
n (males) | 425; (%) | 194; (%)
Abnormal Ejaculation; (mostly ejaculatory delay) | 6.1 | 1
Libido Decreased | 3.8 | <1
Impotence | 2.8 | <1

In female depressed patients receiving citalopram, the reported incidence of decreased libido and anorgasmia was 1.3% (n=638 females) and 1.1% (n=252 females), respectively.

Weight Changes

Patients treated with citalopram in controlled trials experienced a weight loss of about 0.5 kg compared to no change for placebo patients.

ECG Changes

In a thorough QT study, citalopram was found to be associated with a dose-dependent increase in the QTc interval.

Electrocardiograms from citalopram (N=802) and placebo (N=241) groups were compared with respect to outliers defined as subjects with QTc changes over 60 msec from baseline or absolute values over 500 msec post-dose, and subjects with heart rate increases to over 100 bpm or decreases to less than 50 bpm with a 25% change from baseline (tachycardic or bradycardic outliers, respectively). In the citalopram group 1.9% of the patients had a change from baseline in QTcF >60 msec compared to 1.2% of the patients in the placebo group. None of the patients in the placebo group had a post-dose QTcF >500 msec compared to 0.5% of the patients in the citalopram group. The incidence of tachycardic outliers was 0.5% in the citalopram group and 0.4% in the placebo group. The incidence of bradycardic outliers was 0.9% in the citalopram group and 0.4% in the placebo group.

Other Adverse Reactions Observed During the Premarketing Evaluation of Citalopram

The following list of adverse reactions does not include reactions that are: 1) included in Table 3 or elsewhere in labeling, 2) for which a drug cause was remote, 3) which were so general as to be uninformative, and those occurring in only one patient.

Adverse reactions are categorized by body system and listed in order of decreasing frequency according to the following definitions: frequent adverse reactions are those occurring on one or more occasions in at least 1/100 patients; infrequent adverse reactions are those occurring in less than 1/100 patients but at least 1/1000 patients; rare reactions are those occurring in fewer than 1/1000 patients.

Cardiovascular - Frequent: tachycardia, postural hypotension, hypotension. Infrequent: hypertension, bradycardia, edema (extremities), angina pectoris, extrasystoles, cardiac failure, flushing, myocardial infarction, cerebrovascular accident, myocardial ischemia. Rare: transient ischemic attack, phlebitis, atrial fibrillation, cardiac arrest, bundle branch block.

Central and Peripheral Nervous System Disorders - Frequent: paresthesia, migraine. Infrequent: hyperkinesia, vertigo, hypertonia, extrapyramidal disorder, leg cramps, involuntary muscle contractions, hypokinesia, neuralgia, dystonia, abnormal gait, hypesthesia, ataxia. Rare: abnormal coordination, hyperesthesia, ptosis, stupor.

Endocrine Disorders - Rare: hypothyroidism, goiter, gynecomastia.

Gastrointestinal Disorders - Frequent: saliva increased, flatulence. Infrequent: gastritis, gastroenteritis, stomatitis, eructation, hemorrhoids, dysphagia, teeth grinding, gingivitis, esophagitis. Rare: colitis, gastric ulcer, cholecystitis, cholelithiasis, duodenal ulcer, gastroesophageal reflux, glossitis, jaundice, diverticulitis, rectal hemorrhage, hiccups.

General - Infrequent: hot flushes, rigors, alcohol intolerance, syncope, influenza-like symptoms. Rare: hay fever.

Hemic and Lymphatic Disorders - Infrequent: purpura, anemia, epistaxis, leukocytosis, leucopenia, lymphadenopathy. Rare: pulmonary embolism, granulocytopenia, lymphocytosis, lymphopenia, hypochromic anemia, coagulation disorder, gingival bleeding.

Metabolic and Nutritional Disorders - Frequent: decreased weight, increased weight. Infrequent: increased hepatic enzymes, thirst, dry eyes, increased alkaline phosphatase, abnormal glucose tolerance. Rare: bilirubinemia, hypokalemia, obesity, hypoglycemia, hepatitis, dehydration.

Musculoskeletal System Disorders - Infrequent: arthritis, muscle weakness, skeletal pain. Rare: bursitis, osteoporosis.

Psychiatric Disorders - Frequent: impaired concentration, amnesia, apathy, depression, increased appetite, aggravated depression, suicide attempt, confusion. Infrequent: increased libido, aggressive reaction, paroniria, drug dependence, depersonalization, hallucination, euphoria, psychotic depression, delusion, paranoid reaction, emotional lability, panic reaction, psychosis. Rare: catatonic reaction, melancholia.

Reproductive Disorders/Female* - Frequent: amenorrhea. Infrequent: galactorrhea, breast pain, breast enlargement, vaginal hemorrhage. *% based on female subjects only: 2955

Respiratory System Disorders - Frequent: coughing. Infrequent: bronchitis, dyspnea, pneumonia. Rare: asthma, laryngitis, bronchospasm, pneumonitis, sputum increased.

Skin and Appendages Disorders - Frequent: rash, pruritus. Infrequent: photosensitivity reaction, urticaria, acne, skin discoloration, eczema, alopecia, dermatitis, skin dry, psoriasis. Rare: hypertrichosis, decreased sweating, melanosis, keratitis, cellulitis, pruritus ani.

Special Senses - Frequent: accommodation abnormal, taste perversion. Infrequent: tinnitus, conjunctivitis, eye pain. Rare: mydriasis, photophobia, diplopia, abnormal lacrimation, cataract, taste loss.

Urinary System Disorders - Frequent: polyuria. Infrequent: micturition frequency, urinary incontinence, urinary retention, dysuria. Rare: facial edema, hematuria, oliguria, pyelonephritis, renal calculus, renal pain.

6.2 Post-Marketing Experience

The following adverse reactions have been identified during post-approval use of citalopram, the racemate, or escitolapram, the S-entantiomer of citalopram. Because these reactions are reported voluntarily from a population of uncertain size, it is not always possible to reliably estimate their frequency or establish a causal relationship to drug exposure.

Blood and Lymphatic System Disorders: hemolytic anemia, thrombocytopenia, prothrombin decreased

Cardiac Disorders: torsade de pointes, ventricular arrhythmia, QT prolonged

Endocrine Disorders: hyperprolactinemia

Eye Disorders: angle-closure glaucoma

Gastrointestinal Disorders: gastrointestinal hemorrhage, pancreatitis

General Disorders and Administrative Site Conditions: withdrawal syndrome

Hepatobiliary Disorders: hepatic necrosis

Immune System Disorders: anaphylaxis, allergic reaction

Musculoskeletal and Connective Tissue Disorders: rhabdomyolysis

Nervous System Disorders: grand mal convulsion(s), myoclonus, choreoathetosis, dyskinesia, akathisia, nystagmus

Pregnancy, Puerperium and Perinatal Conditions: spontaneous abortion

Psychiatric Disorders: delirium

Renal and Urinary Disorders: acute renal failure

Reproductive System and Breast Disorders: priapism

Respiratory, thoracic and mediastinal disorders: anosmia, hyposmia

Skin and Subcutaneous Tissue Disorders: Stevens Johnson Syndrome, epidermal necrolysis, angioedema, erythema multiforme, ecchymosis

Vascular Disorders: thrombosis

7 DRUG INTERACTIONS

Table 5 presents clinically important drug interactions with Citalopram Capsules.

Table 5: Clinically Important Drug Interactions with Citalopram Capsules

Monoamine Oxidase Inhibitors (MAOIs)
Clinical Impact: |  | Concomitant use of SSRIs, including Citalopram Capsules, and MAOIs increases the risk of serotonin syndrome.
Intervention: |  | Citalopram Capsules is contraindicated in patients taking MAOIs, including MAOIs such as linezolid or intravenous methylene blue [see Dosage and Administration (2.3), Contraindications (4), Warnings and Precautions (5.3)].
Pimozide
Clinical Impact: | Concomitant use of citalopram with pimozide increases plasma concentrations of pimozide, a drug with a narrow therapeutic index, and may increase the risk of QT prolongation and/or ventricular arrhythmias compared to use of citalopram alone [see Clinical Pharmacology (12.3)].
Intervention: | Citalopram Capsules is contraindicated in patients taking pimozide [see Contraindications (4), Warnings and Precautions (5.2)].
Drugs that Prolong the QTc Interval
Clinical Impact: | Concomitant use of citalopram with drugs that prolong QT can cause additional QT prolongation compared to the use of citalopram alone [see Clinical Pharmacology (12.3)].
Intervention: | Avoid concomitant use of Citalopram Capsules with drugs that prolong the QT interval (Citalopram Capsules is contraindicated in patients taking pimozide) [see Contraindications (4), Warnings and Precautions (5.2)].
CYP2C19 Inhibitors
Clinical Impact: | Concomitant use of citalopram with CYP2C19 inhibitors increases the risk of QT prolongation and/or ventricular arrhythmias compared to the use of citalopram alone [see Clinical Pharmacology (12.3)].
Intervention: | Avoid concomitant use of Citalopram Capsules with CYP2C19 inhibitors [see Warnings and Precautions (5.2)].
Other Serotonergic Drugs
Clinical Impact: | Concomitant use of Citalopram Capsules with other serotonergic drugs (including other SSRIs, SNRIs, triptans, tricyclic antidepressants, opioids, lithium, buspirone, amphetamines, tryptophan, and St. John's Wort) increases the risk of serotonin syndrome.
Intervention: | Monitor patients for signs and symptoms of serotonin syndrome, particularly during Citalopram Capsules initiation and changes in citalopram dosage. If serotonin syndrome occurs, consider discontinuation of Citalopram Capsules and/or concomitant serotonergic drugs [see Dosage and Administration (2.1, 2.4), Warnings and Precautions (5.3)].
Drugs That Interfere With Hemostasis (antiplatelet agents and anticoagulants)
Clinical Impact: | Concomitant use of citalopram and an antiplatelet or anticoagulant may potentiate the risk of bleeding.
Intervention: | Inform patients of the increased risk of bleeding associated with the concomitant use of Citalopram Capsules and antiplatelet agents and anticoagulants. For patients taking warfarin, carefully monitor the international normalized ratio [see Warnings and Precautions (5.4)].

8 USE IN SPECIFIC POPULATIONS

8.1 Pregnancy

Pregnancy Exposure Registry

There is a pregnancy exposure registry that monitors pregnancy outcomes in women exposed to antidepressants during pregnancy. Healthcare providers are encouraged to register patients by calling the National Pregnancy Registry for Antidepressants at 1-844-405-6185 or visiting online at https://womensmentalhealth.org/research/pregnancyregistry/antidepressants.

Risk Summary

Based on data from published observational studies, exposure to SSRIs, particularly in the month before delivery, has been associated with a less than 2-fold increase in the risk of postpartum hemorrhage [see Warnings and Precautions (5.4) and Clinical Considerations].

Available data from published epidemiologic studies and postmarketing reports with citalopram use in pregnancy have not established an increased risk of major birth defects or miscarriage. Published studies demonstrated that citalopram levels in both cord blood and amniotic fluid are similar to those observed in maternal serum. There are risks of persistent pulmonary hypertension of the newborn (PPHN) (see Data) and/or poor neonatal adaptation with exposure to selective serotonin reuptake inhibitors (SSRIs), including Citalopram Capsules, during pregnancy. There also are risks associated with untreated depression in pregnancy (see Clinical Considerations).

In animal reproduction studies, citalopram caused adverse embryo/fetal effects at doses that caused maternal toxicity (see Data).

The estimated background risk of major birth defects and miscarriage for the indicated population is unknown. All pregnancies have a background risk of birth defect, loss, or other adverse outcomes. In the U.S. general population, the estimated background risk of major birth defects and miscarriage in the clinically recognized pregnancies is 2% to 4% and 15% to 20%, respectively.

Clinical Considerations

Disease-Associated Maternal and/or Embryo/Fetal Risk

Women who discontinue antidepressants during pregnancy are more likely to experience a relapse of major depression than women who continue antidepressants. This finding is from a prospective longitudinal study of 201 pregnant women with a history of major depressive disorder who were euthymic and taking antidepressants at the beginning of pregnancy. Consider the risk of untreated depression when discontinuing or changing treatment with antidepressant medication during pregnancy and postpartum.

Maternal Adverse Reactions

Use of Citalopram Capsules in the month before delivery may be associated with an increased risk of postpartum hemorrhage [see Warnings and Precautions (5.4)].

Fetal/Neonatal Adverse Reactions

Neonates exposed to citalopram and other SSRIs late in third trimester have developed complications requiring prolonged hospitalization, respiratory support, and tube feeding. Such complications can arise immediately upon delivery. Reported clinical findings have included respiratory distress, cyanosis, apnea, seizures, temperature instability, feeding difficulty, vomiting, hypoglycemia, hypotonia, hypertonia, hyperreflexia, tremor, jitteriness, irritability, and constant crying. These findings are consistent with either a direct toxic effect of SSRIs or possibly, a drug discontinuation syndrome. It should be noted that, in some cases, the clinical picture is consistent with serotonin syndrome [see Warnings and Precautions (5.3)].

Data

Human Data

Exposure during late pregnancy to SSRIs may have an increased risk for persistent pulmonary hypertension of the newborn (PPHN). PPHN occurs in 1- 2 per 1,000 live births in the general population and is associated with substantial neonatal morbidity and mortality.

Animal Data

Citalopram was administered orally to pregnant rats during the period of organogenesis at doses of 32, 56, and 112 mg/kg/day, which are approximately 8, 14, and 27 times the Maximum Recommended Human Dose (MRHD) of 40 mg, based on mg/m^2 body surface area. Citalopram caused maternal toxicity of CNS clinical signs and decreased weight gain at 112 mg/kg/day, which is 27 times the MRHD. At this maternally toxic dose, citalopram decreased embryo/fetal growth and survival and increased fetal abnormalities (including cardiovascular and skeletal defects). The no observed adverse effect level (NOAEL) for maternal and embryofetal toxicity is 56 mg/kg/day, which is approximately 14 times the MRHD.

Citalopram was administered orally to pregnant rabbits during the period of organogenesis at doses up to 16 mg/kg/day, which is approximately 8 times the MRHD of 40 mg, based on mg/m^2 body surface area. No maternal or embryofetal toxicity was observed. The NOAEL for maternal and embryofetal toxicity is 16 mg/kg/day, which is approximately 8 times the MRHD.

Citalopram was administered orally to pregnant rats during late gestation and lactation periods at doses of 4.8, 12.8, and 32 mg/kg/day, which are approximately 1, 3, and 8 times the MRHD of 40 mg, based on mg/m^2 body surface area. Citalopram increased offspring mortality during the first 4 days of birth and decreased offspring growth at 32 mg/kg/day, which is approximately 8 times the MRHD. The NOAEL for developmental toxicity is 12.8 mg/kg/day, which is approximately 3 times the MRHD. In a separate study, similar effects on offspring mortality and growth were seen when dams were treated throughout gestation and early lactation at doses ≥ 24 mg/kg/day, which is approximately 6 times the MRHD. A NOAEL was not determined in that study.

8.2 Lactation

Risk Summary

Data from the published literature report the presence of citalopram in human milk at relative infant doses ranging between 0.7 to 9.4% of the maternal weight-adjusted dosage and a milk/plasma ratio ranging between 0.78 to 4.3. There are reports of breastfed infants exposed to citalopram experiencing irritability, restlessness, excessive somnolence, decreased feeding, and weight loss (see Clinical Considerations). There is no information about effects of citalopram on milk production.

The developmental and health benefits of breastfeeding should be considered along with the mother’s clinical need for Citalopram Capsules and any potential adverse effects on the breastfed child from Citalopram Capsules or from the underlying maternal condition.

Clinical Considerations

Monitor breastfeeding infants for adverse reactions, such as irritability, restlessness, excessive somnolence, decreased feeding, and weight loss.

8.4 Pediatric Use

The safety and effectiveness of citalopram have not been established in pediatric patients.

Two placebo-controlled trials in 407 pediatric patients with MDD have been conducted with other another formulation of citalopram, and the data were not sufficient to support use in pediatric patients.

Antidepressants increase the risk of suicidal thoughts and behaviors in pediatric patients [see Boxed Warning, Warnings and Precautions (5.1)]. Decreased appetite and weight loss have been observed in association with the use of SSRIs in pediatric patients.

8.5 Geriatric Use

Citalopram Capsules is not recommended for use in the elderly because dosage adjustments are not possible with the available strengths of Citalopram Capsules.

In two pharmacokinetic studies, citalopram AUC was increased by 23% and 30%, respectively, in subjects ≥ 60 years of age as compared to younger subjects, and its half-life was increased by 30% and 50%, respectively.

Of 4,422 patients in clinical studies of citalopram, 1357 were 60 and over, 1034 were 65 and over, and 457 were 75 and over.

SSRIs, including citalopram, have been associated with cases of clinically significant hyponatremia in elderly patients, who may be at greater risk for this adverse reaction [see Warnings and Precautions (5.9)].

8.6 Hepatic Impairment

Citalopram Capsules is not recommended in patients with hepatic impairment. Citalopram oral clearance was reduced by 37% and half-life was doubled in patients with reduced hepatic function compared to normal subjects [see Clinical Pharmacology (12.3)].

Dosage adjustments are not possible with the available strengths of Citalopram Capsules.

9 DRUG ABUSE AND DEPENDENCE

9.1 Controlled Substance

Citalopram is not a controlled substance.

9.2 Abuse

Animal studies suggest that the abuse liability of citalopram is low. Citalopram has not been systematically studied in humans for its potential for abuse, tolerance, or physical dependence. The premarketing clinical experience with citalopram did not reveal any drug-seeking behavior. However, these observations were not systematic and it is not possible to predict, on the basis of this limited experience, the extent to which a CNS-active drug will be misused, diverted, and/or abused once marketed. Consequently, health care providers should carefully evaluate citalopram patients for history of drug abuse and follow such patients closely, observing them for signs of misuse or abuse (e.g., development of tolerance, incrementations of dose, drug-seeking behavior).

10 OVERDOSAGE

The following have been reported with citalopram tablet overdosage:

- Seizures, which may be delayed, and altered mental status including coma.
- Cardiovascular toxicity, which may be delayed, including QRS and QTc interval prolongation, wide complex tachyarrhythmias, and torsade de pointes. Hypertension most commonly seen, but rarely can see hypotension alone or with co‐ingestants including alcohol.
- Serotonin syndrome (patients with a multiple drug overdosage with other proserotonergic drugs may have a higher risk).

Prolonged cardiac monitoring is recommended in Citalopram Capsules overdosage ingestions due to the arrhythmia risk. Gastrointestinal decontamination with activated charcoal should be considered in patients who present early after a Citalopram Capsules overdose.

Consider contacting a Poison Center (1‐800‐221‐2222) or a medical toxicologist for additional overdosage management recommendations.

11 DESCRIPTION

Citalopram Capsules contain citalopram, a selective serotonin reuptake inhibitor (SSRI). Citalopram hydrobromide is a racemic bicyclic phthalane derivative designated (±)-1-(3-dimethylaminopropyl)-1-(4-fluorophenyl)-1,3-dihydroisobenzofuran-5carbonitrile, hydrobromide with the following structural formula:

The molecular formula is C20H22BrFN2O and its molecular weight is 405.35.

Citalopram hydrobromide is a white to almost white crystalline powder. Citalopram hydrobromide is freely soluble in chloroform and sparingly soluble in ethanol and water.

Citalopram Capsules is for oral administration and contains 30 mg of citalopram, equivalent to 37.5 mg of citalopram hydrobromide. The strengths reflect citalopram base equivalent content.

Citalopram Capsules also contain the inactive ingredients copovidone, croscarmellose sodium, gelatin, magnesium stearate, microcrystalline cellulose, talc and titanium dioxide. The capsule shells contain the colorants FD&C Blue #1 and FD&C Red #3.

12 CLINICAL PHARMACOLOGY

12.1 Mechanism of Action

The mechanism of action of citalopram as an antidepressant is unclear, but is presumed to be related to potentiation of serotonergic activity in the central nervous system (CNS) resulting from its inhibition of CNS neuronal reuptake of serotonin (5-HT).

12.2 Pharmacodynamics

In vitro and in vivo studies in animals suggest that citalopram is a selective serotonin reuptake inhibitor (SSRI) with minimal effects on norepinephrine (NE) and dopamine (DA) neuronal reuptake.

Citalopram has no or very low affinity for 5-HT1A, 5-HT2A, dopamine D1 and D2, α1-, α2-, and β-adrenergic, histamine H1, gamma aminobutyric acid (GABA), muscarinic cholinergic, and benzodiazepine receptors.

Cardiac Electrophysiology

Individually corrected QTc (QTcNi) interval was evaluated in a randomized, placebo and active (moxifloxacin 400 mg) controlled cross-over, escalating multiple-dose study in 119 healthy subjects. The maximum mean (upper bound of the 95% one-sided confidence interval) difference from placebo were 8.5 (10.8) and 18.5 (21.0) msec for 20 mg and 60 citalopram, respectively. Based on the established exposure-response relationship, the predicted QTcNi change from placebo (upper bound of the 95% one-sided confidence interval) under the Cmax for the dose of 40 mg is 12.6 (14.3) msec [see Warnings and Precautions (5.2)].

12.3 Pharmacokinetics

Biotransformation of citalopram is mainly hepatic, with a mean terminal half-life of about 52.7 hours (30 mg capsule). With once daily dosing, steady state plasma concentrations are achieved within approximately one week. At steady state, the extent of accumulation of citalopram in plasma, based on the half-life, is expected to be 2.5 times the plasma concentrations observed after a single dose.

Absorption

Following a single oral dose (30 mg capsule) of citalopram, peak blood levels occur at about 3.5 hours. The absolute bioavailability of citalopram was about 80% relative to an intravenous dose.

Effect of Food

Administration of citalopram capsules with a high-fat and high calorie breakfast did not have a significant effect on exposure of citalopram. However, median Tmax of citalopram is delayed by approximately 1 hour (6 vs 5 hours).

Distribution

The volume of distribution of citalopram is about 12 L/kg and the binding of citalopram (CT), demethylcitalopram (DCT) and didemethylcitalopram (DDCT) to human plasma proteins is about 80%.

Elimination

Metabolism

Citalopram is metabolized to demethylcitalopram (DCT), didemethylcitalopram (DDCT), citalopram-N-oxide, and a deaminated propionic acid derivative. In humans, unchanged citalopram is the predominant compound in plasma. At steady state, the concentrations of citalopram's metabolites, DCT and DDCT, in plasma are approximately one-half and one-tenth, respectively, that of the parent drug. In vitro studies show that citalopram is at least 8 times more potent than its metabolites in the inhibition of serotonin reuptake, suggesting that the metabolites evaluated do not likely contribute significantly to the antidepressant actions of citalopram.

In vitro studies using human liver microsomes indicated that CYP3A4 and CYP2C19 are the primary isozymes involved in the N-demethylation of citalopram.

Excretion

Following intravenous administrations of citalopram, the fraction of drug recovered in the urine as citalopram and DCT was about 10% and 5%, respectively. The systemic clearance of citalopram was 330 mL/min, with approximately 20% of that due to renal clearance.

Specific Populations

Geriatric Patients

Citalopram pharmacokinetics in subjects 60 years of age were compared to younger subjects in two normal volunteer studies. In a single-dose study, citalopram AUC and half-life were increased in the subjects 60 years old by 30% and 50%, respectively, whereas in a multiple-dose study they were increased by 23% and 30%, respectively [see Warnings and Precautions (5.2), Use in Specific Populations (8.5)].

Male and Female Patients

In three pharmacokinetic studies (total N=32), citalopram AUC in women was one and a half to two times that in men. This difference was not observed in five other pharmacokinetic studies (total N=114). In clinical studies, no differences in steady state serum citalopram levels were seen between men (N=237) and women (N=388). There were no gender differences in the pharmacokinetics of DCT and DDCT.

Patients with Hepatic Impairment

Citalopram oral clearance was reduced by 37% and half-life was doubled in patients with reduced hepatic function compared to normal subjects [see Warnings and Precautions (5.2)].

Patients with Renal Impairment

In patients with mild to moderate renal impairment, oral clearance of citalopram was reduced by 17% compared to normal subjects. No adjustment of dosage for such patients is recommended. No information is available about the pharmacokinetics of citalopram in patients with severe renal impairment (creatinine clearance < 20 mL/min).

CYP2C19 Poor Metabolizers

In CYP2C19 poor metabolizers, citalopram steady state Cmax and AUC was increased by 68% and 107%, respectively [see Warnings and Precautions (5.2)].

CYP2D6 Poor Metabolizers

Citalopram steady state levels were not significantly different in poor metabolizers and extensive metabolizers of CYP2D6.

Drug Interaction Studies

In vitro enzyme inhibition data did not reveal an inhibitory effect of citalopram on CYP3A4, -2C9, or -2E1, but did suggest that it is a weak inhibitor of CYP1A2, -2D6, and -2C19. Citalopram would be expected to have little inhibitory effect on in vivo metabolism mediated by these enzymes. However, in vivo data to address this question are limited.

CYP3A4 and CYP2C19 Inhibitors

Since CYP3A4 and CYP2C19 are the primary enzymes involved in the metabolism of citalopram, it is expected that potent inhibitors of CYP3A4 (e.g., ketoconazole, itraconazole, and macrolide antibiotics) and inhibitors of CYP2C19 (e.g., omeprazole, cimetidine) might decrease the clearance of citalopram. However, coadministration of citalopram and the potent CYP3A4 inhibitor ketoconazole did not significantly affect the pharmacokinetics of citalopram [see Warnings and Precautions (5.2), Drug Interactions (7)].

Cimetidine

In subjects who had received 21 days of 40 mg/day citalopram, combined administration of 400 mg twice a day cimetidine for 8 days resulted in an increase in citalopram AUC and Cmax of 43% and 39%, respectively [see Warnings and Precautions (5.2), Drug Interactions (7)].

CYP2D6 Inhibitors

Coadministration of a drug that inhibits CYP2D6 with citalopram is unlikely to have clinically significant effects on citalopram metabolism, based on the study results in CYP2D6 poor metabolizers.

Digoxin

In subjects who had received 21 days of 40 mg/day citalopram, combined administration of citalopram and digoxin (single dose of 1 mg) did not significantly affect the pharmacokinetics of either citalopram or digoxin.

Lithium

Coadministration of citalopram (40 mg/day for 10 days) and lithium (30 mmol/day for 5 days) had no significant effect on the pharmacokinetics of citalopram or lithium.

Pimozide

In a controlled study, a single dose of pimozide 2 mg co-administered with citalopram 40 mg given once daily for 11 days was associated with a mean increase in QTc values of approximately 10 msec compared to pimozide given alone. Citalopram did not alter the mean AUC or Cmax of pimozide. The mechanism of this pharmacodynamic interaction is not known [see Contraindications (4), Warnings and Precautions (5.2)].

Theophylline

Combined administration of citalopram (40 mg/day for 21 days) and the CYP1A2 substrate theophylline (single dose of 300 mg) did not affect the pharmacokinetics of theophylline. The effect of theophylline on the pharmacokinetics of citalopram was not evaluated.

Warfarin

Administration of 40 mg/day citalopram for 21 days did not affect the pharmacokinetics of warfarin, a CYP3A4 substrate. Prothrombin time was increased by 5%, the clinical significance of which is unknown.

Carbamazepine

Combined administration of citalopram (40 mg/day for 14 days) and carbamazepine (titrated to 400 mg/day for 35 days) did not significantly affect the pharmacokinetics of carbamazepine, a CYP3A4 substrate. Although trough citalopram plasma levels were unaffected, given the enzyme-inducing properties of carbamazepine, the possibility that carbamazepine might increase the clearance of citalopram should be considered if the two drugs are coadministered.

Triazolam

Combined administration of citalopram (titrated to 40 mg/day for 28 days) and the CYP3A4 substrate triazolam (single dose of 0.25 mg) did not significantly affect the pharmacokinetics of either citalopram or triazolam.

Ketoconazole

Combined administration of citalopram (40 mg) and ketoconazole (200 mg) decreased the Cmax and AUC of ketoconazole by 21% and 10%, respectively, and did not significantly affect the pharmacokinetics of citalopram.

Metoprolol

Administration of 40 mg/day citalopram for 22 days resulted in a two-fold increase in the plasma levels of the beta-adrenergic blocker metoprolol. Increased metoprolol plasma levels have been associated with decreased cardioselectivity. Coadministration of citalopram and metoprolol had no clinically significant effects on blood pressure or heart rate.

Imipramine and Other Tricyclic Antidepressants (TCAs)

In vitro studies suggest that citalopram is a relatively weak inhibitor of CYP2D6. Coadministration of citalopram (40 mg/day for 10 days) with the TCA imipramine (single dose of 100 mg), a substrate for CYP2D6, did not significantly affect the plasma concentrations of imipramine or citalopram. However, the concentration of the imipramine metabolite desipramine was increased by approximately 50%. The clinical significance of the desipramine change is unknown.

13 NONCLINICAL TOXICOLOGY

13.1 Carcinogenesis, Mutagenesis, Impairment Of Fertility

Carcinogenesis

Citalopram increased the incidence of small intestine carcinoma in rats treated for 24 months at doses of 8 and 24 mg/kg/day in the diet, which are approximately 2 and 6 times the Maximum Recommended Human Dose (MRHD) of 40 mg, respectively, based on mg/m^2 body surface area. A no-effect level (NOEL) for this finding was not established.

Citalopram did not increase the incidence of tumors in mice treated for 18 months at doses up 240 mg/kg/day in the diet, which is approximately 30 times the MRDH of 40 mg based on mg/m^2 body surface area.

Mutagenesis

Citalopram was mutagenic in the in vitro bacterial reverse mutation assay (Ames test) in 2 of 5 bacterial strains (Salmonella TA98 and TA1537) in the absence of metabolic activation. It was clastogenic in the in vitro Chinese hamster lung cell assay for chromosomal aberrations in the presence and absence of metabolic activation. Citalopram was not mutagenic in the in vitro mammalian forward gene mutation assay (HPRT) in mouse lymphoma cells or in in vitro/in vivo unscheduled DNA synthesis (UDS) assay in rat liver. It was not clastogenic in the in vitro chromosomal aberration assay in human lymphocytes or in two in vivo mouse micronucleus assays.

Impairment of Fertility

Citalopram was administered orally to female and male rats at doses of 32, 48, and 72 mg/kg/day prior to and throughout mating and continuing to gestation. These doses are approximately 8, 12, and 17 times the MRHD of 40 mg based on mg/m^2 body surface area. Mating and fertility were decreased at doses ≥ 32 mg/kg/day, which is approximately 8 times the MRHD. Gestation duration was increased at 48 mg/kg/day, which is approximately 12 times the MRHD.

13.2 Animal Toxicology and/or Pharmacology

Retinal Changes in Rats

Pathologic changes (degeneration/atrophy) were observed in the retinas of albino rats in the 2-year carcinogenicity study with citalopram. There was an increase in both incidence and severity of retinal pathology in both male and female rats receiving 80 mg/kg/day, which is approximately 19 times the MRHD of 40 mg based on mg/m^2 body surface area. Similar findings were not present in rats treated for two years at the dose of 24 mg/kg/day, in mice treated for 18 months at doses up to 240 mg/kg/day, or in dogs treated for one year at doses up to 20 mg/kg/day, which are approximately 6, 29, and 17 times the MRHD, respectively, based on mg/m^2 body surface area.

Additional studies to investigate the mechanism for this pathology have not been performed, and the potential significance of this effect in humans has not been established.

14 CLINICAL STUDIES

The efficacy of Citalopram Capsules for the treatment for major depressive disorder (MDD) in adult patients is based upon adequate and well-controlled studies of another citalopram product. The results of these adequate and well-controlled studies of citalopram are presented below.

The efficacy of citalopram was established in two placebo-controlled studies (of 4 to 6 weeks in duration) in adult outpatients (ages 18-66) meeting DSM-III or DSM-III-R criteria for major depression (Studies 1 and 2).

Study 1, a 6-week trial in which patients received fixed citalopram doses of 10 mg, 20 mg, 40 mg, and 60 mg daily, showed that citalopram at doses of 40 mg and 60 mg daily (1.5 times the maximum recommended daily dosage of citalopram) was effective as measured by the Hamilton Depression Rating Scale (HAMD) total score, the primary efficacy endpoint. The HAMD-17 is a 17-item, clinician-rated scale used to assess severity of depressive symptoms. Scores on the HAMD-17 range from 0 to 52, with higher scores indicating more severe depression. This study showed no clear effect of the 10 mg and 20 mg daily doses, and the 60 mg daily dose was not more effective than the 40 mg daily dose. Due to the risk of QTc prolongation and ventricular arrhythmias, the maximum recommended dosage of citalopram is 40 mg once daily.

In study 2, a 4-week, placebo-controlled trial in patients with MDD, the initial dose was 20 mg daily, followed by titration to the maximum tolerated dose or a maximum dose of 80 mg daily (2 times the recommended daily dosage of citalopram). Patients treated with citalopram showed significantly greater improvement than placebo patients on the HAMD total score, the primary efficacy endpoint. In three additional placebo-controlled trials in patients with MDD, the difference in response to treatment between patients receiving citalopram and patients receiving placebo was not statistically significant.

In two long-term studies, patients with MDD who had responded to citalopram during an initial 6 or 8 weeks of acute treatment were randomized to continuation of citalopram or placebo. In one study, patients received fixed doses of citalopram 20 mg or 40 mg daily and in the second study, patients received flexible doses of citalopram 20 mg to 60 mg daily (1.5 times the maximum recommended daily dosage for citalopram). In both studies, patients receiving continued citalopram treatment experienced statistically significantly lower relapse rates over the subsequent 6 months compared to those receiving placebo. In the fixed-dose study, the decreased rate of depression relapse was similar in patients receiving 20 mg or 40 mg daily of citalopram. Due to the risk of QTc prolongation and ventricular arrhythmias, the maximum recommended dosage of citalopram is 40 mg once daily.

Analyses of the relationship between treatment outcome and age, gender, and race did not suggest any differential responsiveness on the basis of these patient characteristics.

16 HOW SUPPLIED/STORAGE AND HANDLING

Citalopram Capsules are supplied as:

30 mg capsules: Hard shell gelatin capsules, with “ALM” printed axially on the blue opaque cap in black ink and “691” printed axially on the white opaque body in black ink:

NDC 52427-691-30 Bottle of 30 capsules

Storage and Handling

Store at 20°C to 25°C (68°F to 77°F); excursions permitted to 15°C to 30°C (59°F to 86°F) [see USP Controlled Room Temperature].

17 PATIENT COUNSELING INFORMATION

Advise the patient to read the FDA-approved patient labeling (Medication Guide).

Suicidal Thoughts and Behaviors

Advise patients, and caregivers to look for the emergence of suicidality, especially during treatment and when the dose is adjusted up or down, and instruct them to report such symptoms to their healthcare provider [see Boxed Warning and Warnings and Precautions (5.1)].

QTc Prolongation and Torsade de Pointes

Advise patients to consult their healthcare provider immediately if they feel faint, lose consciousness, or have heart palpitations. Instruct patients to inform their healthcare provider that they are taking Citalopram Capsules before taking any new medications [see Warnings and Precautions (5.2)].

Serotonin Syndrome

Caution patients about the risk of serotonin syndrome, particularly with the concomitant use of Citalopram Capsules with other serotonergic drugs including triptans, tricyclic antidepressants, opioids, lithium, amphetamines, tryptophan, buspirone, St. John’s Wort, and with drugs that impair metabolism of serotonin (in particular, MAOIs, both those intended to treat psychiatric disorders and also others, such as linezolid). Instruct patients to contact their health care provider or report to the emergency room if they experience signs or symptoms of serotonin syndrome [see Warnings and Precautions (5.3), Drug Interactions (7)].

Increased Risk of Bleeding

Inform patients about the concomitant use of Citalopram Capsules with aspirin, NSAIDs, other antiplatelet drugs, warfarin, or other anticoagulants because the combined use has been associated with an increased risk of bleeding. Advise patients to inform their health care provider if they are taking or are planning to take any prescription or over-the-counter medications that increase the risk of bleeding [see Warnings and Precautions (5.4)].

Activation of Mania or Hypomania

Advise patients and their caregivers to observe for signs of activation of mania/hypomania and instruct them to report such symptoms to the healthcare provider [see Warnings and Precautions (5.5)].

Discontinuation Syndrome

Advise patients not to abruptly discontinue Citalopram Capsules and to discuss any tapering regimen with their healthcare provider. Inform patients that adverse reactions can occur when Citalopram Capsules is discontinued [see Warnings and Precautions (5.6)].

Sexual Dysfunction

Advise patients that use of Citalopram Capsules may cause symptoms of sexual dysfunction in both male and female patients. Inform patients that they should discuss any changes in sexual function and potential management strategies with their healthcare provider [see Warnings and Precautions (5.10)].

Pregnancy

- Advise pregnant women to notify their healthcare providers if they become pregnant or intend to become pregnant during treatment with Citalopram Capsules.
- Advise patients that Citalopram Capsules use late in pregnancy may lead to an increased risk for neonatal complications requiring prolonged hospitalization, respiratory support, tube feeding, and/or persistent pulmonary hypertension of the newborn (PPHN) [see Use in Specific Populations (8.1)].
- Advise women that there is a pregnancy exposure registry that monitors pregnancy outcomes in women exposed to citalopram during pregnancy [see Use in Specific Populations (8.1)].

Lactation

Advise breastfeeding women to monitor infants for excess sedation, restlessness, agitation, poor feeding and poor weight gain and to seek medical care if they notice these signs [see Use in Specific Populations (8.2)].

Distributed by:
Almatica Pharma LLC
Morristown, NJ 07960 USA

PI691-01

MEDICATION GUIDE

Citalopram (sye tal' oh pram) Capsules

for oral use

What is the most important information I should know about Citalopram Capsules?

Citalopram Capsules may cause serious side effects, including:

- Increased risk of suicidal thoughts and actions. Citalopram Capsules and other antidepressant medicines may increase suicidal thoughts and actions in some children, adolescents, and young adults, especially within the first few months of treatment or when the dose is changed. Citalopram Capsules is not for use in children.
  - Depression or other mental illnesses are the most important causes of suicidal thoughts and actions.
    How can I watch for and try to prevent suicidal thoughts and actions in myself or a family member?
  - Pay close attention to any changes, especially sudden changes in mood, behavior, thoughts, or feelings, or if you develop suicidal thoughts or actions. This is very important when an antidepressant medicine is started or when the dose is changed.
  - Call your healthcare provider right away to report new or sudden changes in mood, behavior, thoughts, or feelings.
  - Keep all follow-up visits with your healthcare provider as scheduled. Call your healthcare provider between visits as needed, especially if you have concerns about symptoms.

Call your healthcare provider or get emergency help right away if you or your family member have any of the following symptoms, especially if they are new, worse, or worry you:

- thoughts about suicide or dying
- new or worse depression
- feeling very agitated or restless
- trouble sleeping (insomnia)
- acting aggressive, being angry, or violent
- an extreme increase in activity and (mania)
- attempts to commit suicide
- new or worse anxiety
- panic attacks
- new or worse irritability
- acting on dangerous impulses
- other unusual changes in behavior or mood

What is Citalopram Capsules?

Citalopram Capsules is a prescription medicine used to treat a certain type of depression called Major Depressive Disorder (MDD) in adults.

It is not known if Citalopram Capsules is safe and effective for use in children.

Who should not take Citalopram Capsules?

Do not take Citalopram Capsules if you:

- take a Monoamine Oxidase Inhibitor (MAOI)
- have stopped taking an MAOI in the last 14 days
- are being treated with the antibiotic linezolid or intravenous methylene blue
- take pimozide
- are allergic to citalopram or any of the ingredients in Citalopram Capsules. See the end of this Medication Guide for a complete list of ingredients in Citalopram Capsules.

Ask your healthcare provider or pharmacist if you are not sure if you take an MAOI, including MAOIs such as linezolid or intravenous methylene blue.

Do not start taking an MAOI for at least 14 days after you stop treatment with Citalopram Capsules.

Before taking Citalopram Capsules, tell your healthcare provider about all your medical conditions, including if you:

- have or had a family history of suicide, depression, bipolar disorder, mania or hypomania
- have an abnormal heart rhythm called QT prolongation
- have or had heart problems, including a heart attack, heart failure, abnormal heart rhythm, or long QT syndrome
- have low potassium, magnesium, or sodium levels in your blood
- have or had bleeding problems
- have or had seizures (convulsions)
- have high pressure in the eye (glaucoma)
- have or had kidney or liver problems
- are pregnant or plan to become pregnant. Citalopram Capsules may harm your unborn baby. Taking Citalopram Capsules late in pregnancy may lead to an increased risk of certain problems in your newborn. Talk to your healthcare provider about the risks and benefits of treating depression during pregnancy.
  - Tell your healthcare provider right away if you become pregnant or think you may be pregnant during treatment with Citalopram Capsules.
  - There is a pregnancy registry for females who are exposed to Citalopram Capsules during pregnancy. The purpose of the registry is to collect information about the health of females exposed to Citalopram Capsules and their baby. If you become pregnant during treatment with Citalopram Capsules, talk to your healthcare provider about registering with the National Pregnancy Registry for Antidepressants. You can register by calling 1-844-405-6185 or visiting online at https://womensmentalhealth.org/research/pregnancyregistry/antidepressants.
- are breastfeeding or plan to breastfeed. Citalopram passes into your breast milk. Talk to your healthcare provider about the best way to feed your baby during treatment with Citalopram Capsules.
  - If you breastfeed during treatment with Citalopram Capsules, tell your healthcare provider right away if your baby develops sleepiness or fussiness, or is not feeding or gaining weight well.

Tell your healthcare provider about all the medicines that you take, including prescription and over-the-counter medicines, vitamins, and herbal supplements.

Citalopram Capsules and other medicines may affect each other causing possible serious side effects. Citalopram Capsules may affect the way other medicines work and other medicines may affect the way Citalopram Capsules works.

Especially tell your healthcare provider if you take:

- medicines used to treat migraine headaches known as triptans
- tricyclic antidepressants
- lithium
- tramadol, fentanyl, meperidine, methadone, or other opioids
- tryptophan
- buspirone
- amphetamines
- St. John’s Wort
- medicines that can affect blood clotting such as aspirin, nonsteroidal anti-inflammatory drugs (NSAIDs) and warfarin
- diuretics
- methadone
- gatifloxacin or moxifloxacin
- medicines used to control your heart rate or rhythm (antiarrhythmics)
- medicines used to treat mood, anxiety, psychotic or thought disorders, including selective serotonin reuptake inhibitors (SSRIs) and serotonin norepinephrine reuptake inhibitors (SNRIs)

Ask your healthcare provider if you are not sure if you are taking any of these medicines. Your healthcare provider can tell you if it is safe to take Citalopram Capsules with your other medicines.

Do not start or stop any other medicines during treatment with Citalopram Capsules without talking to your healthcare provider first. Stopping Citalopram Capsules suddenly may cause you to have serious side effects. See, “What are the possible side effects of Citalopram Capsules?”

Know the medicines you take. Keep a list of them to show to your healthcare provider and pharmacist when you get a new medicine.

How should I take Citalopram Capsules?

- Take Citalopram Capsules exactly as your healthcare provider tells you to take it. Do not change your dose or stop taking Citalopram Capsules without first talking to your healthcare provider.
- Your healthcare provider may need to change the dose of Citalopram Capsules until it is the right dose for you.
- Take Citalopram Capsules 1 time each day with or without food.
- If you take too much Citalopram Capsules,call your healthcare provider or poison control center at 1-800-222-1222 or go to the nearest hospital emergency room right away.

What are the possible side effects of Citalopram Capsules?

Citalopram Capsules may cause serious side effects, including:

- See “What is the most important information I should know about Citalopram Capsules?”
- Heart rhythm problems. Citalopram Capsules may cause a serious change in your heartbeat (a fast or irregular heartbeat) that may cause death. Tell your healthcare provider right away if you feel faint or pass out, or if you have a change in your heartbeat.
- Serotonin syndrome. Taking Citalopram Capsules can cause a potentially life-threatening problem called serotonin syndrome. The risk of developing serotonin syndrome is increased when Citalopram Capsules is taken with certain other medicines. See, “Who should not take Citalopram Capsules?” Call your healthcare provider or go to the nearest hospital emergency room right away if you have any of the following signs and symptoms of serotonin syndrome:
  - agitation
  - confusion
  - fast heartbeat
  - dizziness
  - flushing
  - tremors, stiff muscles, or muscle twitching
  - seizures
  - Seeing or hearing things that are not real (hallucinations)
  - coma
  - blood pressure changes
  - sweating
  - high body temperature (hyperthermia)
  - loss of coordination
  - nausea, vomiting, diarrhea
- Increased risk of bleeding. Taking Citalopram Capsules with aspirin, non-steroidal anti-inflammatory drugs (NSAIDs), warfarin or blood thinners may add to this risk. Tell your healthcare provider right away about any unusual bleeding or bruising.
- Manic episodes. Manic episodes may happen in people with bipolar disorder who take Citalopram Capsules. Symptoms may include:
  - greatly increased energy
  - racing thoughts
  - unusually grand ideas
  - talking more or faster than usual
  - severe trouble sleeping
  - reckless behavior
  - excessive happiness or irritability
- Discontinuation syndrome. Suddenly stopping Citalopram Capsules may cause you to have serious side effects. Your healthcare provider may want to decrease your dose slowly. Symptoms may include:
  - nausea
  - irritability and agitation
  - electric shock sensation (paresthesia)
  - confusion
  - headache
  - problems sleeping
  - ringing in your ears (tinnitus)
  - changes in your mood
  - dizziness
  - anxiety
  - sweating
  - tiredness
  - hypomania
  - seizures
- Seizures (convulsions).
- Eye problems (angle-closure glaucoma). Many antidepressant medicines, including Citalopram Capsules, may cause a certain type of eye problem called angle-closure glaucoma. Call your healthcare provider if you have changes in your vision or eye pain.
- Low sodium levels in your blood (hyponatremia). Low sodium levels in your blood may be serious and may cause death. Elderly people may be at greater risk for this. Tell your healthcare provider right away if you develop any signs or symptoms of low sodium levels in your blood during treatment with Citalopram Capsules. Signs and symptoms of low sodium levels in your blood may include:
  - headache
  - memory changes
  - weakness and unsteadiness on your feet which can lead to falls
  - difficulty concentrating
  - confusion
    In severe or more sudden cases, signs and symptoms include:
  - hallucinations (seeing or hearing things that are not real)
  - seizures
  - stopping breathing
  - fainting
  - coma
  - death
- Sexual problems (dysfunction). Taking selective serotonin reuptake inhibitors (SSRIs), including Citalopram Capsules, may cause sexual problems that are common but may be serious.
  Symptoms in males may include:
  - Delayed ejaculation or inability to have an ejaculation
  - Decreased sex drive
  - Problems getting or keeping an erection
    Symptoms in females may include:
  - Decreased sex drive
  - Delayed orgasm or inability to have an orgasm
    Talk to your healthcare provider if you develop any changes in your sexual function or if you have any questions or concerns about sexual problems during treatment with Citalopram Capsules. There may be treatments your healthcare provider can suggest.

The most common side effects of Citalopram Capsules include:

- fever
- muscle aches and pain
- agitation
- swelling of your sinuses
- joint stiffness
- not feeling hungry (anorexia)
- yawning

These are not all the possible side effects of Citalopram Capsules.

Call your doctor for medical advice about side effects. You may report side effects to FDA at 1-800-FDA-1088.

How should I store Citalopram Capsules?

- Store Citalopram Capsules at room temperature between 68°F to 77°F (20°C to 25°C).
- Keep Citalopram Capsules and all medicines out of the reach of children.

General information about the safe and effective use of Citalopram Capsules.

Medicines are sometimes prescribed for purposes other than those listed in a Medication Guide. Do not use Citalopram Capsules for a condition for which it was not prescribed.Do not give Citalopram Capsules to other people, even if they have the same symptoms that you have. It may harm them. You may ask your healthcare provider or pharmacist for information about Citalopram Capsules that is written for healthcare professionals.

What are the ingredients in Citalopram Capsules?

Active ingredient: citalopram hydrobromide

Inactive ingredients: copovidone, croscarmellose sodium, gelatin, magnesium stearate, microcrystalline cellulose, talc and titanium dioxide. The capsule shells contain the colorants FD&C Blue #1 and FD&C Red #3.

Distributed by: Almatica Pharma LLC, Morristown, NJ 07960 USA

For more information about Citalopram Capsules, call 1-877-447-7979.

This Medication Guide has been approved by the U.S. Food and Drug Administration. Revised: 8/2023

MG691-01

LABEL - PRINCIPAL DISPLAY PANEL

NDC 52427-691-30

Citalopram Capsules

30 mg

PHARMACIST: Dispense the accompanying Medication Guide to each patient.

30 Capsules

For oral use

Rx only